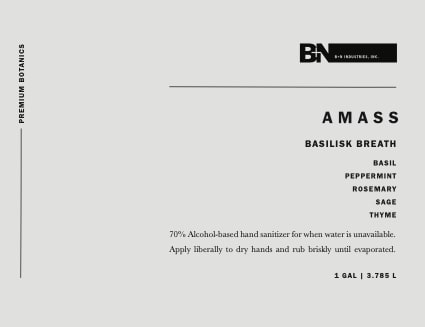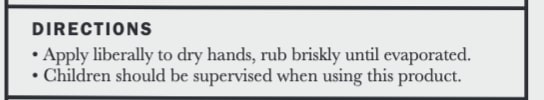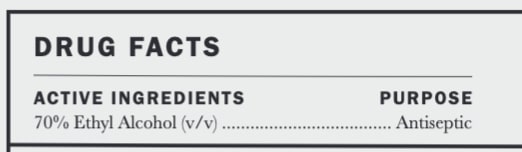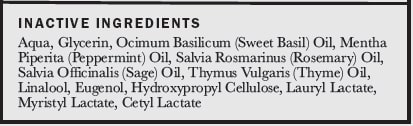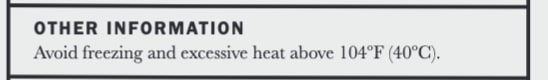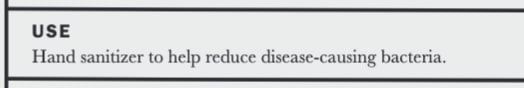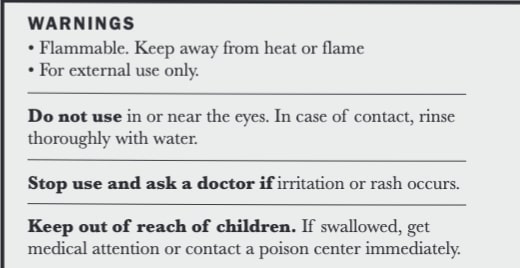 DRUG LABEL: AMASS Basilisk Breath Hand Sanitizer Serum
NDC: 77419-2003 | Form: GEL
Manufacturer: AMASS Brands, Inc
Category: otc | Type: HUMAN OTC DRUG LABEL
Date: 20200905

ACTIVE INGREDIENTS: ALCOHOL 2.781 L/3.785 L
INACTIVE INGREDIENTS: SAGE OIL; HYDROXYPROPYL CELLULOSE (90000 WAMW); WATER; CETYL LACTATE; BASIL OIL; LINALOOL, (+/-)-; MYRISTYL LACTATE; LAURYL LACTATE; GLYCEROL FORMAL; PEPPERMINT OIL; ROSEMARY OIL; THYME OIL; EUGENOL

Active Ingredients ......... Purpose
70% Ethyl Alcohol (v/v)........ Antiseptic

use

Do not use in or near the eyes. In case of contact, rinse thoroughly with water.

Keep out of reach of children. If swallowed, get medical attention or contact a poison center immediately.

USE
Hand sanitizer to help reduce disease-causing bacteria

Stop use and ask a doctor if irriation or rash occurs.

Directions
Apply liberally to dry hands, rub briskly until evaporated
Children should be supervised when using this product

OTHER INFORMATION
Avoid freezing and excessive heat above 104F (40C)

WARNINGS
Flammable. Keep away from heat or flame.
For external use only.
Do not use in or near the eyes. In case of contact, rinse thoroughly with water.
Stop use and ask a doctor if irritation or rash occurs.
Keep out of reach of children. IF swallowed, get medical attention or contact a poison center immediately.

DIRECTIONS
Apply liberally to dry hands, rub briskly until evaporated.
Children should be supervised when using this product

INACTIVE INGREDIENTS
Aqua, Glycerin, Ocimum Basilicum (Sweet Basil) Oil, Mentha Piperita (Peppermint) Oil, Salvia Rosmarinus (Rosemary) Oil, Salvia Officinalis (Sage) Oil, Thymus Vulgaris (Thyme) Oil, Linalool, Eugenol, Hydroxypropyl Cellulose, Lauryl Lactate, Myristyl Lactate, Cetyle Lactate

DIRECTIONS
Apply liberally to dry hands, rub briskly until evaporated.
Children should be supervised when using this product

WARNINGS
Flammable. Keep away from heat or flame.
For external use only.
Do not use in or near the eyes. In case of contact, rinse thoroughly with water.
Stop use and ask a doctor if irritation or rash occurs.
Keep out of reach of children. IF swallowed, get medical attention or contact a poison center immediately.

USE
Hand sanitizer to help reduce disease-causing bacteria.

PACKAGE LABEL

B+N

AMASS
BASILISK BREATH
BASIL
PEPPERMINT
ROSEMARY
SAGE
THYME
70% Alcohol-based hand sanitizer for when water is not available. Manufactured in Los Angeles, California.
1 gal 3.785L

---------------------------- Premium Botanics